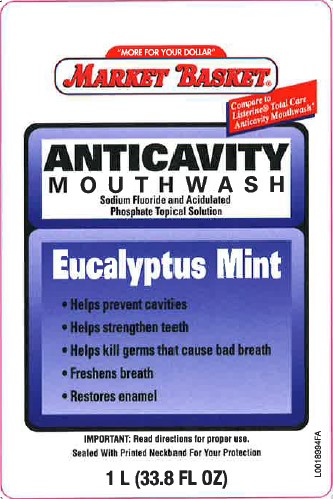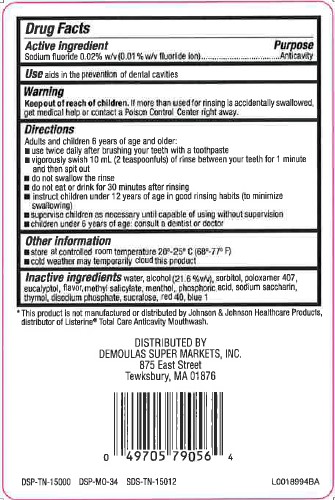 DRUG LABEL: Anticavity
NDC: 53942-163 | Form: MOUTHWASH
Manufacturer: Demoulas Super Markets, Inc.
Category: otc | Type: HUMAN OTC DRUG LABEL
Date: 20260203

ACTIVE INGREDIENTS: SODIUM FLUORIDE 0.2 mg/1 mL
INACTIVE INGREDIENTS: WATER; ALCOHOL; SORBITOL; POLOXAMER 407; EUCALYPTOL; METHYL SALICYLATE; MENTHOL; PHOSPHORIC ACID; SACCHARIN SODIUM; THYMOL; SODIUM PHOSPHATE, DIBASIC, ANHYDROUS; SUCRALOSE; FD&C RED NO. 40; FD&C BLUE NO. 1

Market Basket 163.005/163AF
Anticavity Mouthwash

Active Ingredient

Sodium fluoride 0.02% w/v (0.01% w/v fluoride ion)

Purpose

Anticavity

Use

aids in the prevention of dental cavities

Warnings

for this product

Keep out of reach of children.

If more than used for rinsing is accidentally swallowed, get medical help or contact a Poison Control Center right away.

Directions

Adults and children 12 years of age and older

- use twice daily after brushing your teeth with a toothpaste
- vigorously swish 10 mL (2 teaspoonfuls) of rinse between your teeth for 1 minute and then spit out
- do not swallow the rinse
- do not eat or drink for 30 minutes after rinsing
- instruct children under 12 years of age in good rinsing habits (to minimize swallowing)
- supervise children as necessary until capable of using without supervision
- children under 6 years of age: consult a dentist or doctor

Other information

• store at controlled room temperature 20⁰ - 25⁰C (68⁰ - 77⁰F)
• cold weather may temporarily cloud this product

Inactive ingredients

water, alcohol (21.6 %v/v), sorbitol, poloxamer 407, eucalyptol, flavor, methyl salicylate, menthol, phosphoric acid, sodium saccharin, thymol, disodium phosphate, sucralose, red 40, blue 1

Disclaimer

*This product is not manufactured or distributed by Johnson & Johnson Healthcare Products, distributor of ListerineTotal Care Anticavity Mouthwash.

ADVERSE REACTION

DISTRIBUTED BY

DEMOULAS SUPER MARKETS, INC

875 EAST STREET

TEWKSBURY, MA 01876

DSP-TN-15000 DSP-MO-34 SDS-TN-15012

principal panel display

"More for your Dollar"

MARKET BASKET®

Compare to Listerine®Total Care Anticavity Mouthwash*

ANTICAVITY

MOUTHWASH

Sodium Fluoride and Acidulated Phosphate Topical Solution

Eucalyptus Mint

• Helps prevent cavities
• Helps strengthen teeth
• Helps kill germs that cause bad breath
• Freshens breath
• Restores enamel

IMPORTANT: Read directions for proper use.

Sealed With Printed Neckband For Your Protection

1 L (33.8 FL OZ)